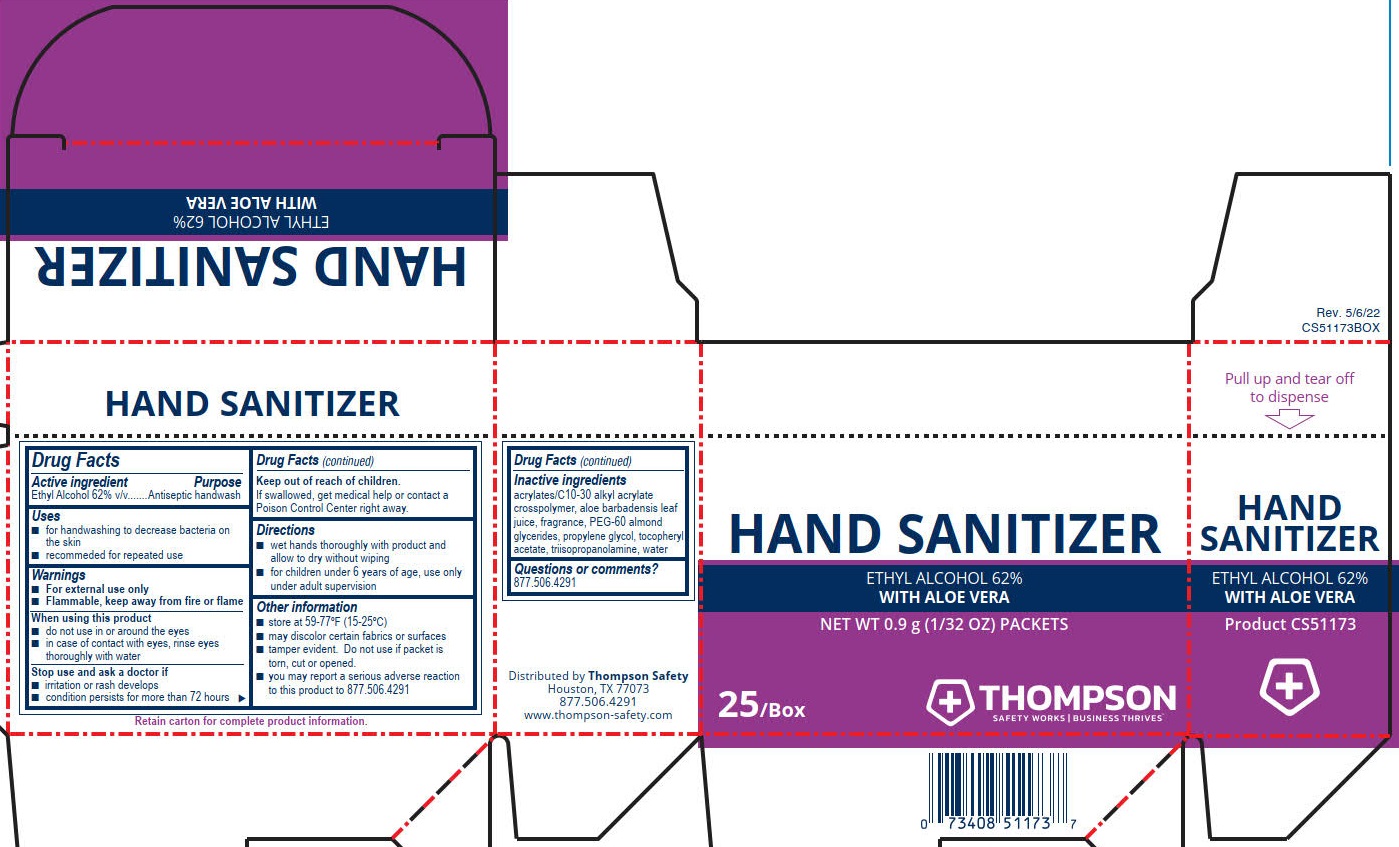 DRUG LABEL: Thompson Hand Sanitizer
NDC: 73408-512 | Form: GEL
Manufacturer: Thompson
Category: otc | Type: HUMAN OTC DRUG LABEL
Date: 20240116

ACTIVE INGREDIENTS: ALCOHOL 62 mL/100 mL
INACTIVE INGREDIENTS: WATER; CARBOMER COPOLYMER TYPE A; TRIISOPROPANOLAMINE; PEG-60 ALMOND GLYCERIDES; PROPYLENE GLYCOL; ALOE VERA LEAF; .ALPHA.-TOCOPHEROL ACETATE, DL-

Thompson Hand Sanitizer

Active ingredient

Ethyl Alcohol 62% v/v

Purpose

Antiseptic handwash

Uses

- for hand washing to decrease bacteria on the skin
- recommended for repeated use

Warnings

- For external use only
- Flammable, keep away from fire or flames

When using this product

- do not use in or around the eyes
- in case of contact with eyes, rinse eyes throroughly with water

Stop use ans ask a doctor if

- irritation or rash develops
- condition persists for more than 72 hours

Keep out of reach of children.

If swallowed, get medical help or contact a Poison Control Center right away.

Directions

- wet hands thoroughly with product and allow to dry without wiping
- for children under 6 years of age, use only under adult supervision

Other information

- store at 59-77ºF (15-25ºC)
- may discolor certain fabrics or surfaces
- tamper evident. Do not use if packet is torn, cut or opened
- you may report a serious adverse reaction to this product to 877.506.4291

Inactive ingredients

acrylates/C10-30 alkyl acrylate crosspolymer, aloe barbadensis leaf juice, fragrance, PEG-60 almond glycerides, propylene glycol, tocopheryl acetate, triisopropanolamine, water

Questions or comments? 877.506.4291

PACKAGE LABEL

Thompson

Hand Sanitizer

Ethyl Alcohol 62%

With Aloe Vera

Net WT 0.9 g (1/32 OZ) Packets

25/Box

Thompson

Safety Works | Buisness Thrives™